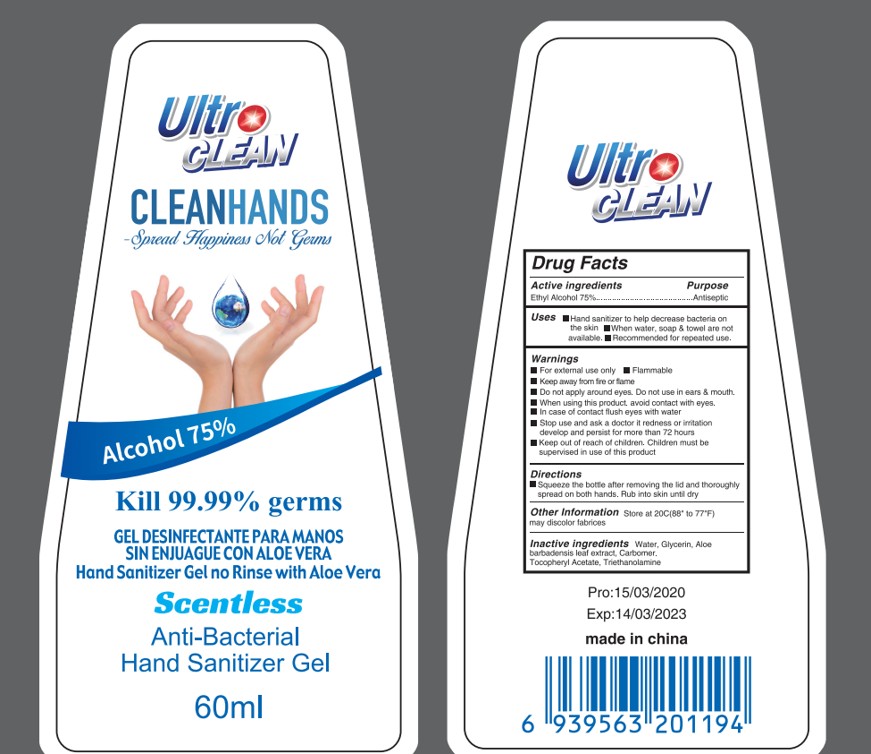 DRUG LABEL: Hand Sanitizer
NDC: 87111-001 | Form: LIQUID
Manufacturer: Zhejiang Hudson Import& Export Co., Ltd
Category: otc | Type: HUMAN OTC DRUG LABEL
Date: 20251009

ACTIVE INGREDIENTS: ALCOHOL 75 g/100 mL
INACTIVE INGREDIENTS: WATER; GLYCERIN; .ALPHA.-TOCOPHEROL ACETATE

87111-001 Hand Sanitizer

ACTIVE INGREDIENT

Ethyil Alcohol 75%

PURPOSE

Antiseptic

Uses
Hand sanitizer to help decrease bacteria on the skin
When water, soap & towel are not available.
Recommended for repeated use.

WARNINGS

For external use only
Flammable
Keep away from fire or flame

Do not apply around eyes.
Do not use in ears & mouth.

When using this product. avoid contact with eyes.
In case of contact flush eyes with water

Stop use and ask a doctor it redness or irritation develop and persist for more than 72 hours

Keep out of reach of children. Children must be supervised in use of this product

DOSAGE AND ADMINISTRATION

Pump as needed into your palms and thoroughly spread on both hands. Rub into skin until dry

INACTIVE INGREDIENT

WATER
Tocopheryl Acetate
GLYERIN